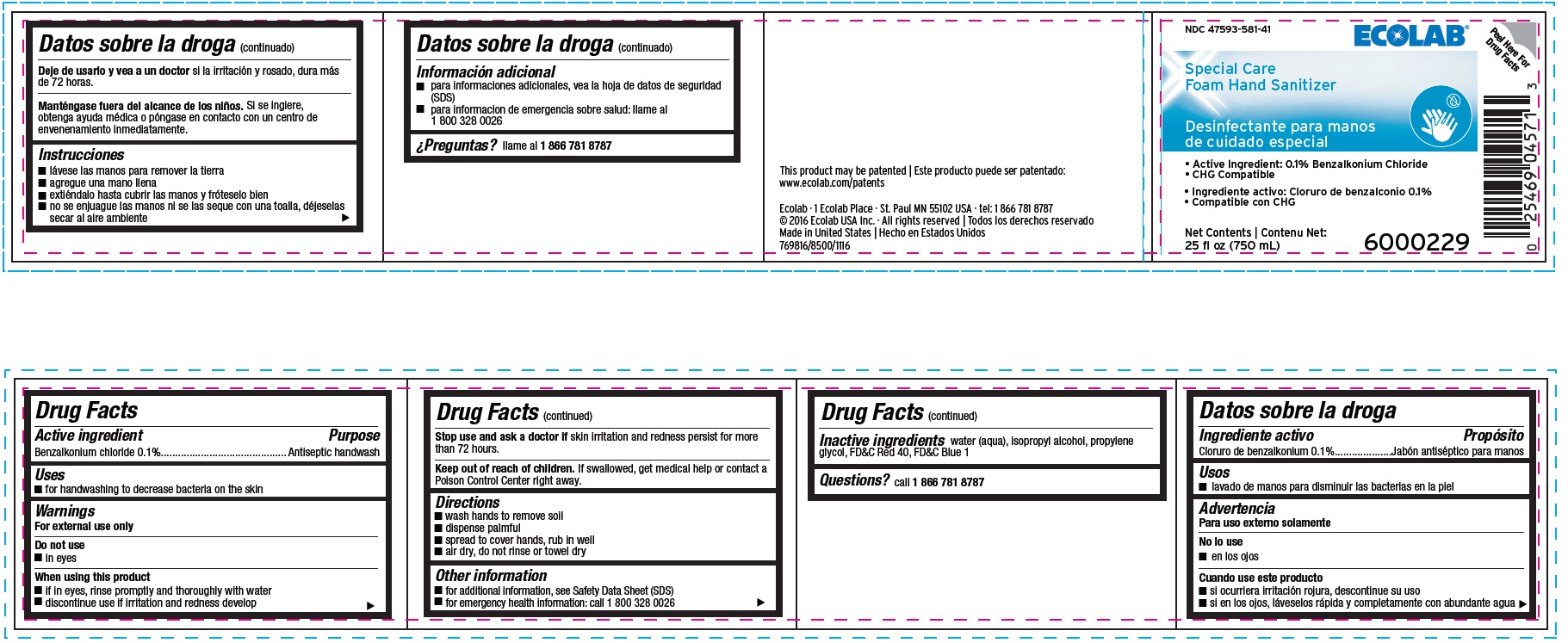 DRUG LABEL: Ecolab
NDC: 47593-581 | Form: SOLUTION
Manufacturer: Ecolab Inc.
Category: otc | Type: HUMAN OTC DRUG LABEL
Date: 20251230

ACTIVE INGREDIENTS: BENZALKONIUM CHLORIDE 1 mg/1 mL
INACTIVE INGREDIENTS: WATER; ISOPROPYL ALCOHOL; PROPYLENE GLYCOL; FD&C RED NO. 40; FD&C BLUE NO. 1

Drug Facts

Active ingredient

Benzalkonium chloride 0.1%

Purpose

Antiseptic handwash

Uses

- for handwashing to decrease bacteria on the skin

Warnings

For external use only

Do not use

- in eyes

When using this product

- if in eyes, rinse promptly and throughly with water
- discontinue use if irritation and redness develop

Stop use and ask doctor if skin irritation or redness persists for more than 72 hours.

Keep out of reach of children. If swallowed, get medical help or contact a Poison Control Center right away.

Directions

- wash hands to remove soil
- dispense palmful
- spread to cover hands, rub in well
- air dry, do not rinse or towel dry

Other information

- for additional information, see Safety Data Sheet (SDS)
- for emergency medical information worldwide, call 1 800 328 0026

INACTIVE INGREDIENT

Inactive ingredients water (aqua), isopropyl alcohol, propylene glycol, FD&C red 40, FD&C blue 1

Questions? call 1 800 781 8787

Representative label and principal display panel

NDC 47593-581-41

ECOLAB

Special Care

Foam Hand Sanitizer

Active Ingredient: Benzalkonium chloride 0.1%

CHG Compatible

Net Contents

25 fl oz (750 mL)

This product may be patented:

www.ecolab.com/patents

Ecolab · 1 Ecolab Place · St. Paul MN 55102 USA · tel: 1 866 781 8787

© 2016 Ecolab USA Inc. · All rights reserved

Made in United States

769816/8500/1116